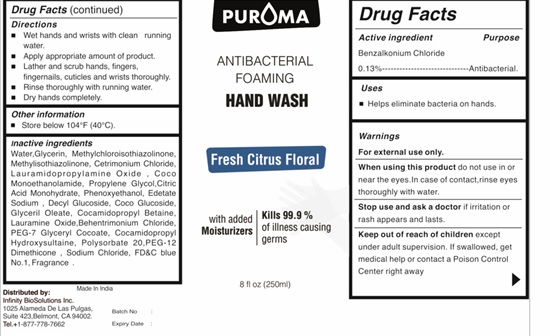 DRUG LABEL: PUROMA  Antibacterial Foaming  Hand Wash  With Fragrance alcohol  Free citrus floral
NDC: 80948-014 | Form: LIQUID
Manufacturer: ZENITH MICRO CONTROL
Category: otc | Type: HUMAN OTC DRUG LABEL
Date: 20231214

ACTIVE INGREDIENTS: BENZALKONIUM CHLORIDE 130 mg/100 mL
INACTIVE INGREDIENTS: WATER; METHYLCHLOROISOTHIAZOLINONE; GLYCERIN; METHYLISOTHIAZOLINONE; CETRIMONIUM CHLORIDE; LAURAMIDOPROPYLAMINE OXIDE; COCO MONOETHANOLAMIDE; PROPYLENE GLYCOL; CITRIC ACID MONOHYDRATE; PHENOXYETHANOL; EDETATE SODIUM; SODIUM CHLORIDE; DECYL GLUCOSIDE; COCO GLUCOSIDE; GLYCERYL OLEATE; COCAMIDOPROPYL BETAINE; LAURAMINE OXIDE; BEHENTRIMONIUM CHLORIDE; PEG-7 GLYCERYL COCOATE; COCAMIDOPROPYL HYDROXYSULTAINE; POLYSORBATE 20; PEG-12 DIMETHICONE; FD&C BLUE NO. 1; FRAGRANCE FRESH CITRUS FLORAL ORC1501495

Active ingredient

Benzalkonium chloride 0.13%

Purpose

Antibacterial

Uses

Helps eliminate bacteria on hands.

Warnings

• For external use only.
• When using this product do not use in or near the eyes. In case of contact, rinse eyes thoroughly with water.
• Stop use and ask a doctor if irritation or rash appears and lasts.

Keep out of reach of children

except under adult supervision. If swallowed, get medical help or contact a Poison Control Center right away.

Directions

• Wet hands and wrists with clean running water.
• Apply appropriate amount of product.
• Lather and scrub hands, fingers, fingernails, cuticles and wrists thoroughly.
• Rinse thoroughly with running water.
• Dry hands completely.

Other information

• Store below 104°F (40°C)

Inactive ingredient

Water,Glycerin, Methylchloroisothiazolinone, Methylisothiazolinone, Cetrimonium Chloride, Lauramidopropylamine Oxide , Coco Monoethanolamide, Propylene Glycol,Citric Acid Monohydrate, Phenoxyethanol, Edetate Sodium , Decyl Glucoside, Coco Glucoside, Glyceril Oleate, Cocamidopropyl Betaine, Lauramine Oxide,Behentrimonium Chloride, PEG-7 Glyceryl Cocoate, Cocamidopropyl Hydroxysultaine, Polysorbate 20, Sodium Chloride, PEG-12 Dimethicone , FD&C Blue NO. 1, Fragrance Fresh Citrus Floral ORC1501495.